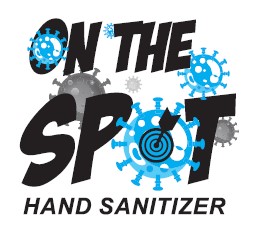 DRUG LABEL: ON THE SPOT HAND SANITIZER
NDC: 77584-100 | Form: GEL
Manufacturer: DCI Binzel Chemical Laboratories
Category: otc | Type: HUMAN OTC DRUG LABEL
Date: 20211231

ACTIVE INGREDIENTS: ALCOHOL 70 mL/100 mL
INACTIVE INGREDIENTS: MYRISTICA FRAGRANS FRUIT 0.0093 mL/100 mL; FD&C BLUE NO. 1 0.00011 mL/100 mL; FRAGRANCE LAVENDER & CHIA F-153480 0.019 mL/100 mL; TRIETHANOLAMINE 2-CYCLOHEXYL-4,6-DINITROPHENOLATE 1.4 mL/100 mL; GLYCERIN 1.1 mL/100 mL; CARBOMER HOMOPOLYMER TYPE A (ALLYL PENTAERYTHRITOL CROSSLINKED) 0.09 mL/100 mL; WATER 27.33 mL/100 mL; VITAMIN D 0.025 mL/100 mL; .ALPHA.-TOCOPHEROL 0.02 mL/100 mL; DENATONIUM BENZOATE 0.0001 mL/100 mL

Drug Facts

Active Ingredient(s)

Active Ingredient: Ethyl Alcohol 70% .............Purpose: Antiseptic

Purpose

Antiseptic, Hand Sanitizer

Uses

Hand sanitizer to help reduce bacteria on the skin

Recommended for repeated use..

Warnings

For external use only. Flammable. Keep away from heat or flame.

- When using this product do not use in or near the eyes.
- In case of contact, rinse eyes thoroughly with water.

WHEN USING

Discontinue use if redness or irritation develops. If condition persists for more than 72 hours, contact a doctor.

STOP USE

Do not drink. Not edible. In case of accidental ingestion, seek professional assistance or contact a Poison Control Center immediately.

Keep out of reach of children.

Children should only use this product under adult supervision.

Directions

- Place enough product in your palm to thoroughly spread on both hands and rub into the skin until dry. Recommended for repeated use.

Other information

- Do not store above 105F.
- May discolor some fabrics.
- Harmful to wood finishes and plastics.

Inactive ingredients

Water, Carbomer, Amyl Methyl Propanol, Glycerin, Fragrance, Vitamins D&E, FD&C Blue No. 1